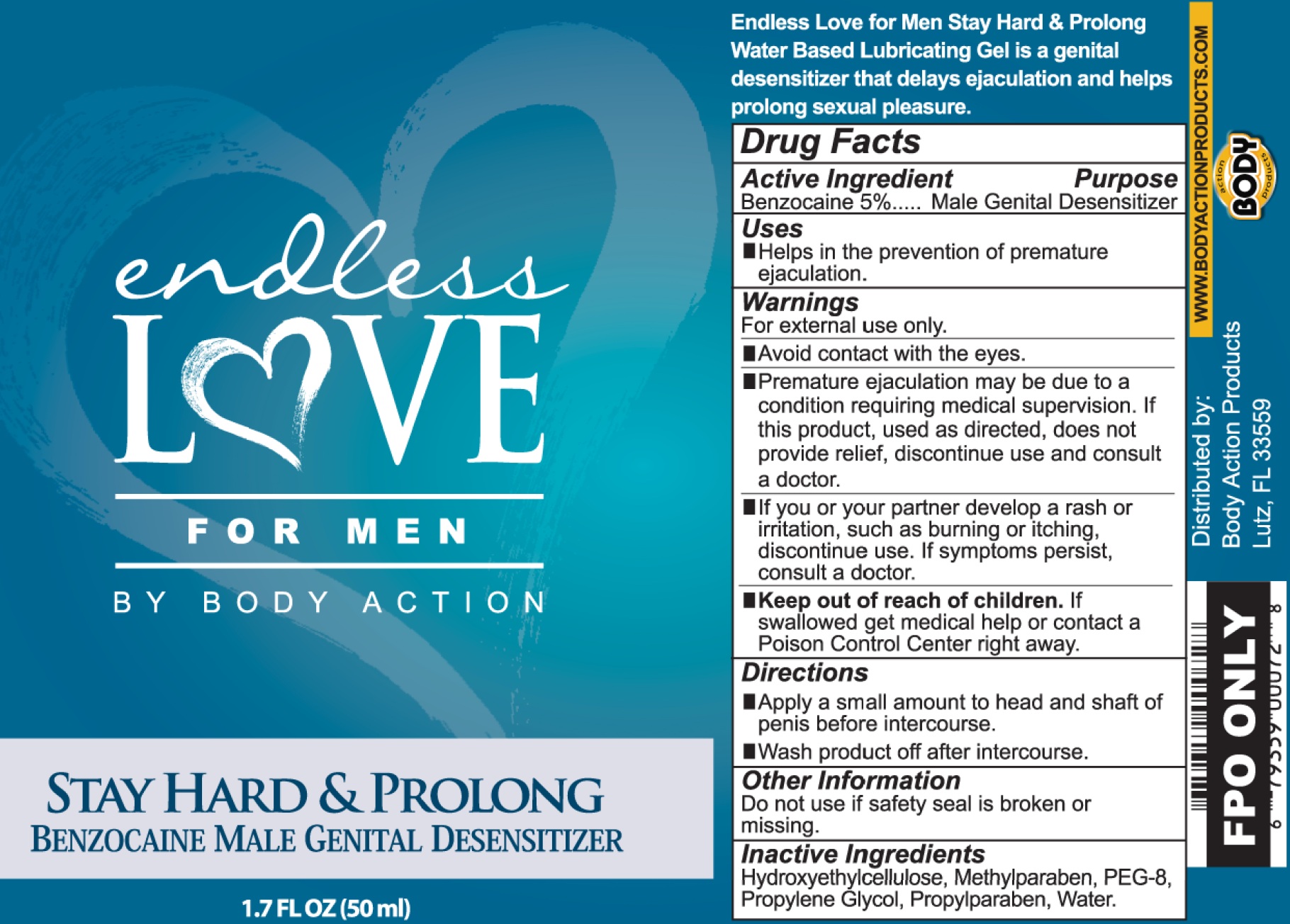 DRUG LABEL: Endless Love For Men
NDC: 70742-360 | Form: GEL
Manufacturer: Body Action Products, Inc
Category: otc | Type: HUMAN OTC DRUG LABEL
Date: 20231110

ACTIVE INGREDIENTS: BENZOCAINE 50 mg/1 mL
INACTIVE INGREDIENTS: METHYLPARABEN; POLYETHYLENE GLYCOL 400; PROPYLENE GLYCOL; PROPYLPARABEN; WATER

Endless Love For Men

Active Ingredient

Benzocaine 5%

Purpose

Male Genital Desensitizer

Uses

- Helps in the prevention of premature ejaculation.

Warnings

For extenal use only.

- Avoid contact with the eyes.
- Premature ejaculation may be due to a condition requiring medial supervision. If this product, used as directed, does not provide relief, discontinue use and consult a doctor.

Keep out of reach of children.

If swallowed get medical help or contact a Poison Control right away.

Directions

- Apply a small amount to head and shaft of penis before intercouse.
- Wash product off after intercourse.

Other Information

Do not use if safery seal is broken or missing.

Inactive Ingredients

Hydroxyethylcellulose, Methylparaben, PEG-8, Propylene Glycol, Propylparaben, Water.